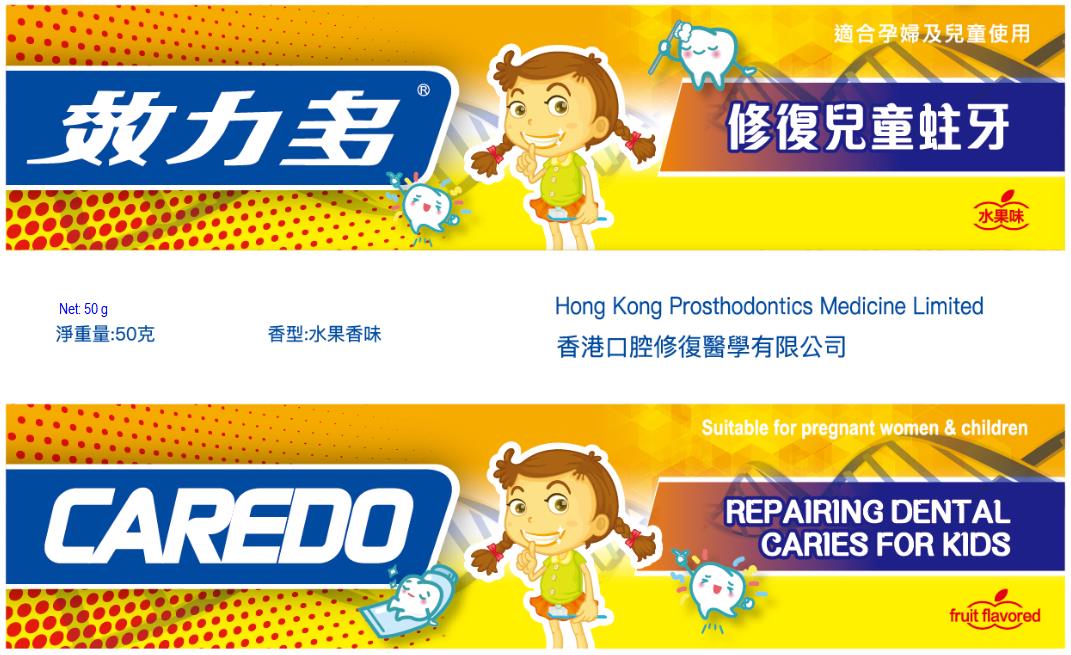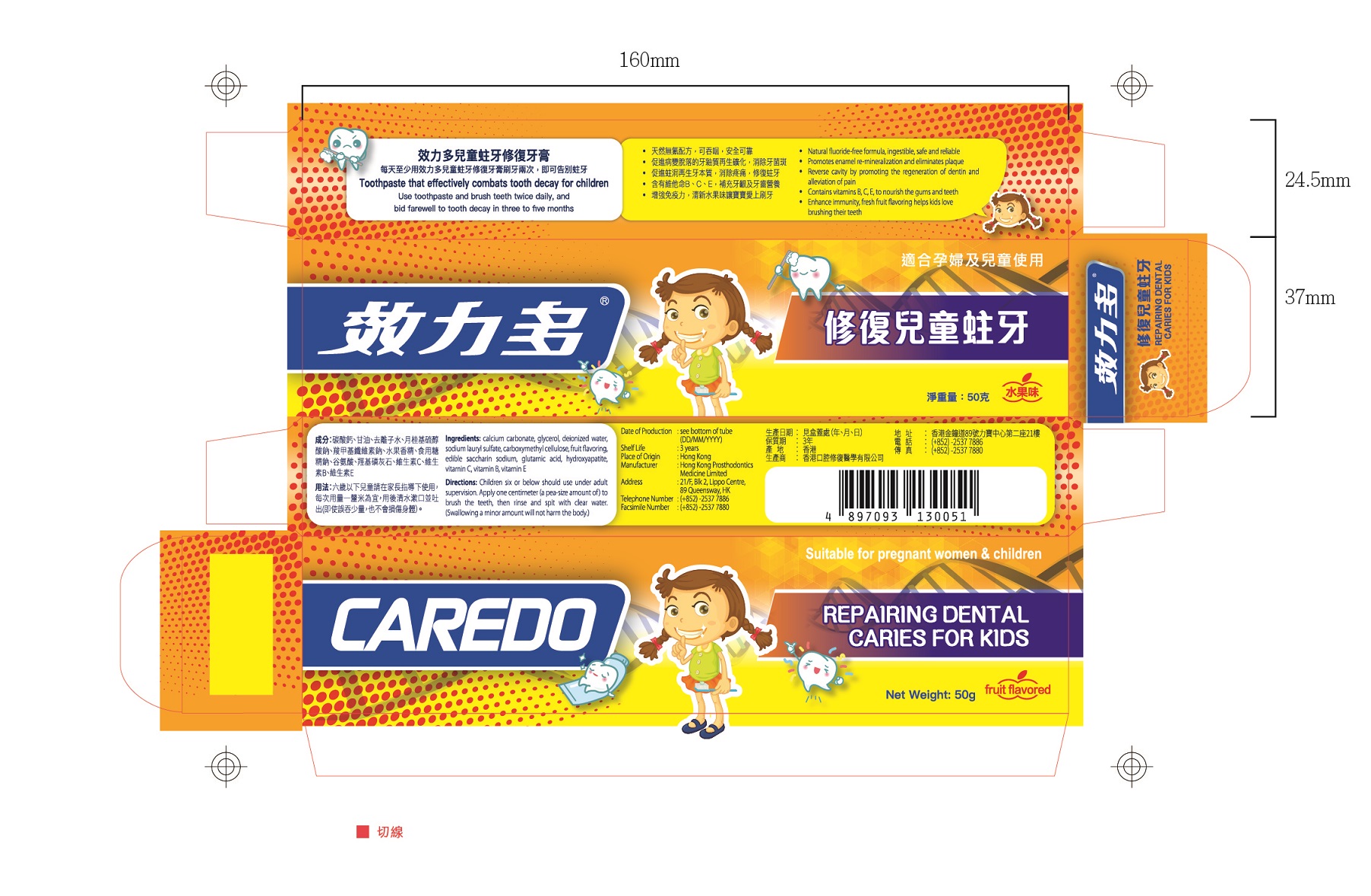 DRUG LABEL: CAREDO Repairing Dental Caries for Kids Toothpastes
NDC: 72415-233 | Form: PASTE, DENTIFRICE
Manufacturer: Hong Kong Prosthodontics Medicine Limited
Category: otc | Type: HUMAN OTC DRUG LABEL
Date: 20180815

ACTIVE INGREDIENTS: CALCIUM PHOSPHATE, UNSPECIFIED FORM 0.25 g/50 g
INACTIVE INGREDIENTS: CARBOXYMETHYLCELLULOSE 0.5 g/50 g; WATER 6.75 g/50 g; CALCIUM CARBONATE 25 g/50 g; SACCHARIN SODIUM 0.05 g/50 g; SODIUM LAURYL SULFATE 1 g/50 g; GLYCERIN 15 g/50 g; MANDARIN OIL 0.75 g/50 g; ASCORBIC ACID 0.15 g/50 g; GLUTAMIC ACID 0.25 g/50 g; PANTOTHENIC ACID 0.15 g/50 g; .ALPHA.-TOCOPHEROL, D- 0.15 g/50 g

CAREDO Repairing Dental Caries for Kids Toothpaste, 50g

Active ingredient

hydroxyapatite (0.5%): 0.25g/package.

Inactive ingredient

calcium carbonate (50%): 25g/package;

glycerol (30%): 15g/package;
deionized water (13.5%): 6.75g/package;
sodium lauryl sulfate (2%): 1g/package;
carboxymethyl cellulose (1%): 0.5g/package;

fruit flavoring (1.5%): 0.75g/package;
edible saccharin sodium (0.1%): 0.05g/package;
glutamic acid (0.5%): 0.25g/package;

vitamin C (0.3%): 0.15g/package;

vitamin B (0.3%): 0.15g/package;

vitamin E (0.3%): 0.15g/package;.

Purpose

Eliminates plaque, reverse cavity, etc.

When using

When want to eliminates plaque, reverse cavity, etc.

Do not use when oral infection.
It should be cautiously used if you are kind of allergic constitution or you have inflammation.

Stop use

If irritation or discomfort occurs, discontinue the use and consult a physician.

Ask doctor

If irritation or discomfort occurs, discontinue the use and consult a physician.

Ask doctor/pharmacist when you current use other drugs.

Keep out of reach of children aged 6 or under.

Children six or below should use under adult supervision.

Apply one centimeter (a pea-size amount of) to brush the teeth, then rinse and spit with clear water.

(Swallowing a minor amount will not harm the body)

Questions

Please contact us when you have any questions.

Pregnancy or breast feeding

Pregnant or breast feeding women allowed to use this product.

Indications & usage

Apply properly this product on the toothbrush, and brush tooth as like common do.

Dosage & administration

One tube of 50g in one package.

Dosage forms & strengths

It is paste form.
Apply proper as you need.

Warnings

Keep out of reach of children aged 6 or under.
Children six or below should use under adult supervision.
Apply one centimeter (a pea-size amount of) to brush the teeth, then rinse and spit with clear water.
(Swallowing a minor amount will not harm the body)

Package label. Principal display panel

---

Container Label

---

---

Package Label

---